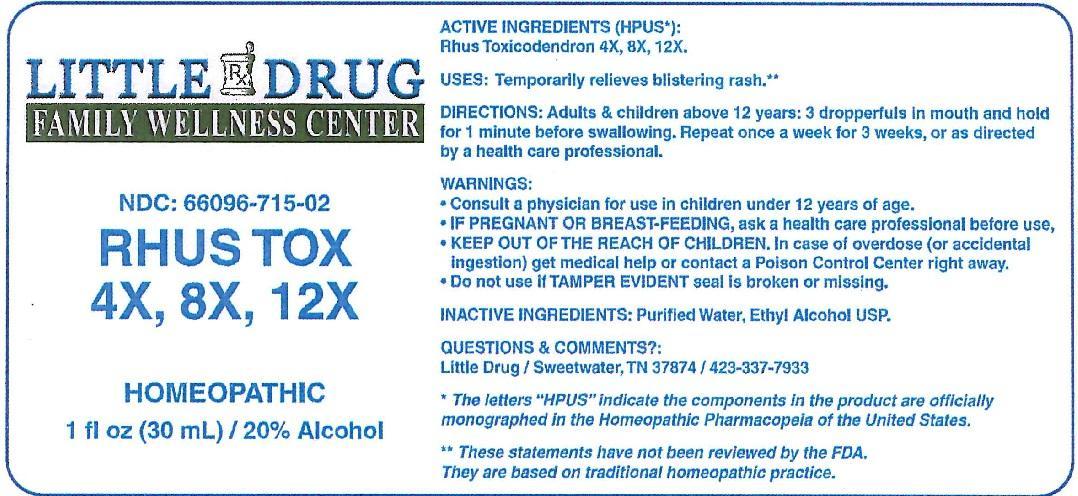 DRUG LABEL: Rhus Tox 4X, 8X, 12X
NDC: 66096-715 | Form: LIQUID
Manufacturer: OHM PHARMA INC.
Category: homeopathic | Type: HUMAN OTC DRUG LABEL
Date: 20170308

ACTIVE INGREDIENTS: TOXICODENDRON PUBESCENS LEAF 4 [hp_X]/30 mL
INACTIVE INGREDIENTS: WATER; ALCOHOL

RHUS TOX 4X, 8X, 12X

ACTIVE INGREDIENTS (HPUS*):

Rhus Toxicodendron 4X, 8X, 12X

* The letters "HPUS" indicate the components in the product are officially monographed in the Homeopathic Pharmacopeia of the United States.

INDICATIONS AND USAGE

USES: Temporarily relieves blistering rash.**

** These statements have not been reviewed by the FDA. They are based on traditional homeopathic practice.

PURPOSE

Temporarily relieves blistering rash.**

DOSAGE AND ADMINISTRATION

DIRECTIONS: Adults & children above 12 years: 3 dropperfulls in mouth and hold for 1 minute before swallowing. Repeat once a week for 3 weeks, or as directed by a health care professional.

WARNINGS:

- Consult a physician for use in children under 12 years of age.
- IF PREGNANT OR BREAST-FEEDING, ask a health care professional before use.
- KEEP OUT OF THE REACH OF CHILDREN. In case of overdose (or accidental ingestion) get medical help or contact a Poison Control Center right away.
- Do not use if TAMPER EVIDENT seal is broken or missing.

Keep out of reach of children.

INACTIVE INGREDIENTS: Purified Water, Ethyl Alcohol USP.

QUESTIONS & COMMENTS?:

Little Drug / Sweetwater, TN 37874 / 423-337-7933

PACKAGE LABEL

LITTLE DRUG

FAMILY WELLNESS CENTER

NDC: 66096-715-02

RHUS TOX

4X, 8X, 12X

HOMEOPATHIC

1 fl oz (30 mL) / 20% Alcohol